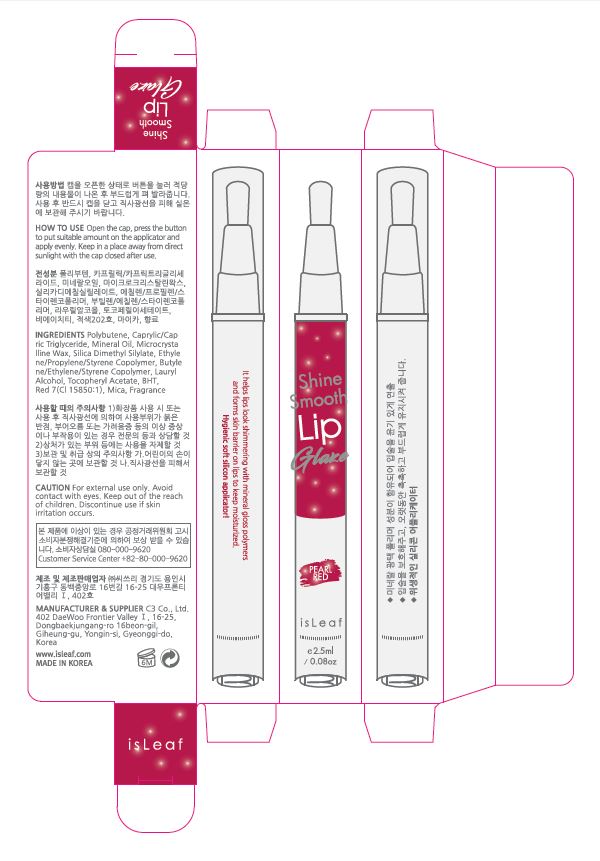 DRUG LABEL: isLeaf Shine Smooth Lip Glaze Pearl Red
NDC: 70818-013 | Form: LIQUID
Manufacturer: C3 Co., Ltd.
Category: otc | Type: HUMAN OTC DRUG LABEL
Date: 20170828

ACTIVE INGREDIENTS: MINERAL OIL 8 g/100 mL
INACTIVE INGREDIENTS: SILICA DIMETHYL SILYLATE 2 g/100 mL

Drug Facts

ACTIVE INGREDIENT

mineral oil

INACTIVE INGREDIENT

polybutene, lauryl alcohol, etc

PURPOSE

skin protectant

keep out of reach of the children

INDICATIONS AND USAGE

Open the cap, press the button to put suitable amount on the applicator and apply evenly. Keep in a place away from direct sunlight with the cap closed after use

WARNINGS

1. If the following symptoms occur after product use, stop using the product immediately and consult a dermatologist (continuous use can exacerbate the symptoms).
1) Occurrence of red spots, swelling, itchiness, and other skin irritation
2) If the symptoms above occur after the application area is exposed to direct sunlight
2. Do not use on open wounds, eczema, and other skin irritations
3. Precaution for Storage and Handling
1) Close the lid after use
2) Keep out of reach of infants and children
3) Do not to store in a place with high/low temperature and exposed to direct sunlight

4. Use as avoiding eye areas.

DOSAGE AND ADMINISTRATION

for external use only